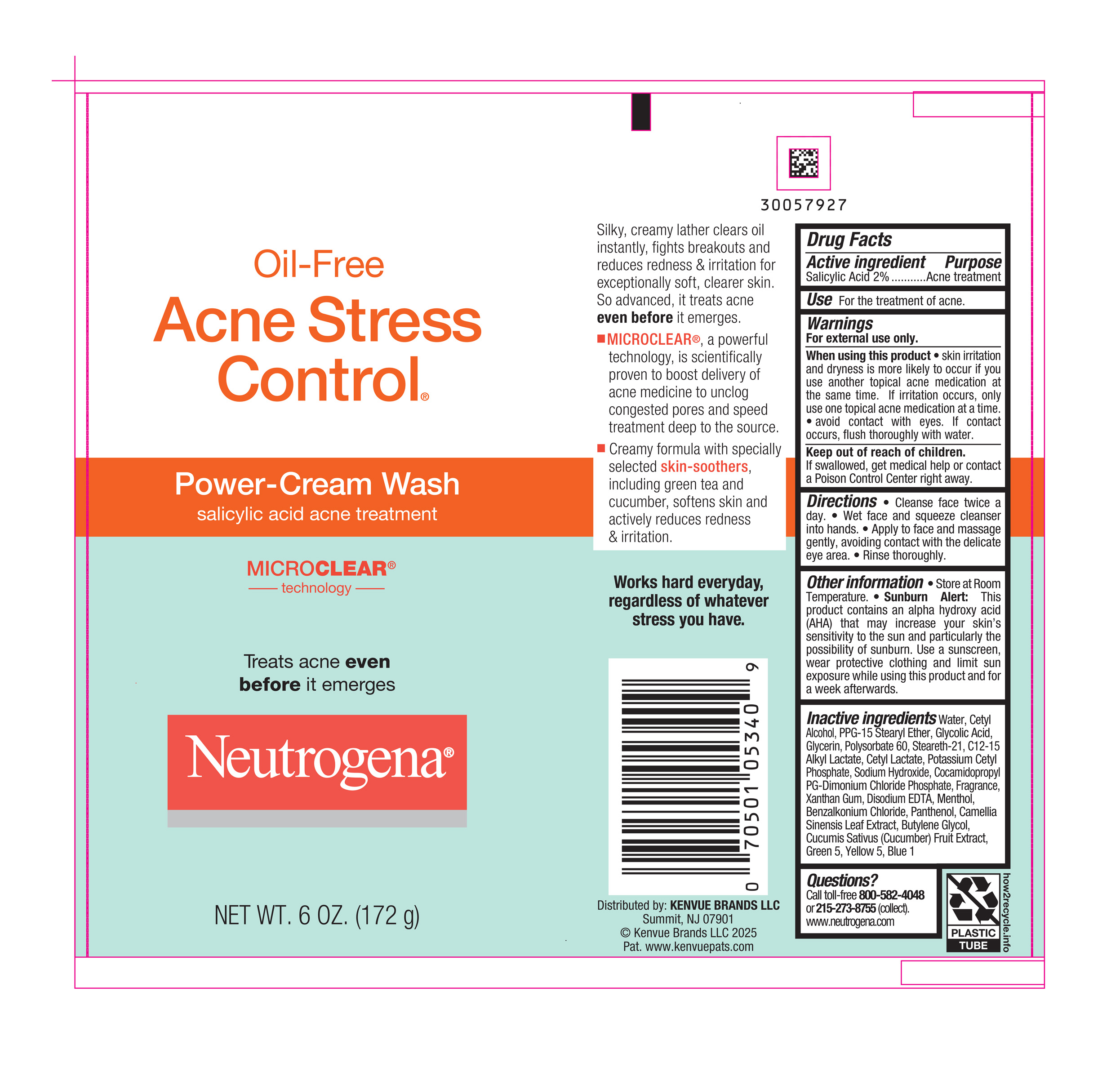 DRUG LABEL: Neutrogena Oil-Free Acne Stress Control Power-Cream Wash
NDC: 69968-0941 | Form: CREAM
Manufacturer: Kenvue Brands LLC
Category: otc | Type: HUMAN OTC DRUG LABEL
Date: 20250818

ACTIVE INGREDIENTS: SALICYLIC ACID 20 mg/1 g
INACTIVE INGREDIENTS: WATER; CETYL ALCOHOL; PPG-15 STEARYL ETHER; GLYCOLIC ACID; GLYCERIN; POLYSORBATE 60; STEARETH-21; C12-15 ALKYL LACTATE; CETYL LACTATE; POTASSIUM CETYL PHOSPHATE; SODIUM HYDROXIDE; COCAMIDOPROPYL PROPYLENE GLYCOL-DIMONIUM CHLORIDE PHOSPHATE; XANTHAN GUM; EDETATE DISODIUM; MENTHOL, UNSPECIFIED FORM; BENZALKONIUM CHLORIDE; PANTHENOL; GREEN TEA LEAF; BUTYLENE GLYCOL; CUCUMBER; D&C GREEN NO. 5; FD&C YELLOW NO. 5; FD&C BLUE NO. 1

Neutrogena Oil-Free Acne Stress Control Power-Cream Wash

Drug Facts

Active ingredient

Salicylic Acid 2%

Purpose

Acne treatment

Use

For the treatment of acne.

Warnings

For external use only.

When using this product • skin irritation and dryness is more likely to occur if you use another topical acne medication at the same time. If irritation occurs, only use one topical acne medication at a time.

• avoid contact with eyes. If contact occurs, flush thoroughly with water.

Keep out of reach of children. If swallowed, get medical help or contact a Poison Control Center right away.

Directions

- Cleanse face twice a day.
- Wet face and squeeze cleanser into hands.
- Apply to face and massage gently, avoiding contact with the delicate eye area.
- Rinse thoroughly.

Other information

• Store at Room Temperature. • Sunburn Alert: This product contains an alpha hydroxy acid (AHA) that may increase your skin’s sensitivity to the sun and particularly the possibility of sunburn. Use a sunscreen, wear protective clothing and limit sun exposure while using this product and for a week afterwards.

Inactive ingredients

Water, Cetyl Alcohol, PPG-15 Stearyl Ether, Glycolic Acid, Glycerin, Polysorbate 60, Steareth-21, C12-15 Alkyl Lactate, Cetyl Lactate, Potassium Cetyl Phosphate, Sodium Hydroxide, Cocamidopropyl PG-Dimonium Chloride Phosphate, Fragrance, Xanthan Gum, Disodium EDTA, Menthol, Benzalkonium Chloride, Panthenol, Camellia Sinensis Leaf Extract, Butylene Glycol, Cucumus Sativus (Cucumber) Fruit Extract, Green 5, Yellow 5, Blue 1

Questions?

Call toll-free 800-582-4048 or 215-273-8755 (collect). www.neutrogena.com

Distributed by:

Kenvue Brands LLC
Summit, NJ 07901

PRINCIPAL DISPLAY PANEL - 172 g Tube Label

Oil-Free

Acne Stress

Control®

Power-Cream Wash

salicylic acid acne treatment

MICRO CLEAR®

technology

Treats acne even

before it emerges

Neutrogena®

NET WT. 6 OZ. (172 g)